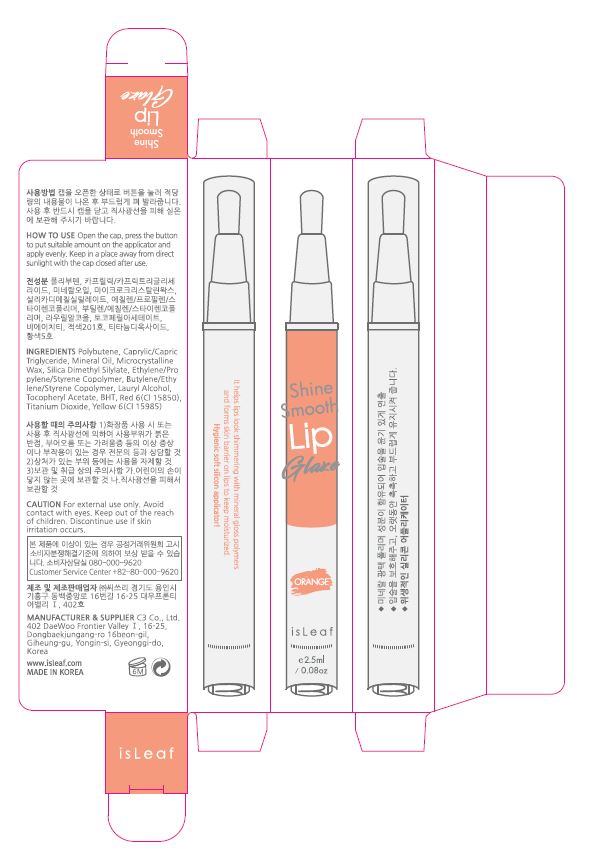 DRUG LABEL: isLeaf Energy Water
NDC: 70818-014 | Form: CREAM
Manufacturer: C3 Co., Ltd.
Category: otc | Type: HUMAN OTC DRUG LABEL
Date: 20170828

ACTIVE INGREDIENTS: GLYCERIN 8 g/100 g
INACTIVE INGREDIENTS: WATER

Drug Facts

ACTIVE INGREDIENT

glycerin

INACTIVE INGREDIENT

water, propylene glycol, dimethicone, etc

PURPOSE

skin protectant

keep out of reach of the children

INDICATIONS AND USAGE

Apply fair amount of Energy Water Cream onto all parts of the face and neck avoiding the eye contour area at the last step of the skin care

WARNINGS

1. If the following symptoms occur after product use, stop using the product immediately and consult a dermatologist (continuous use can exacerbate the symptoms).
1) Occurrence of red spots, swelling, itchiness, and other skin irritation
2) If the symptoms above occur after the application area is exposed to direct sunlight
2. Do not use on open wounds, eczema, and other skin irritations
3. Precaution for Storage and Handling
1) Close the lid after use
2) Keep out of reach of infants and children
3) Do not to store in a place with high/low temperature and exposed to direct sunlight

4. Use as avoiding eye areas.

DOSAGE AND ADMINISTRATION

for external use only